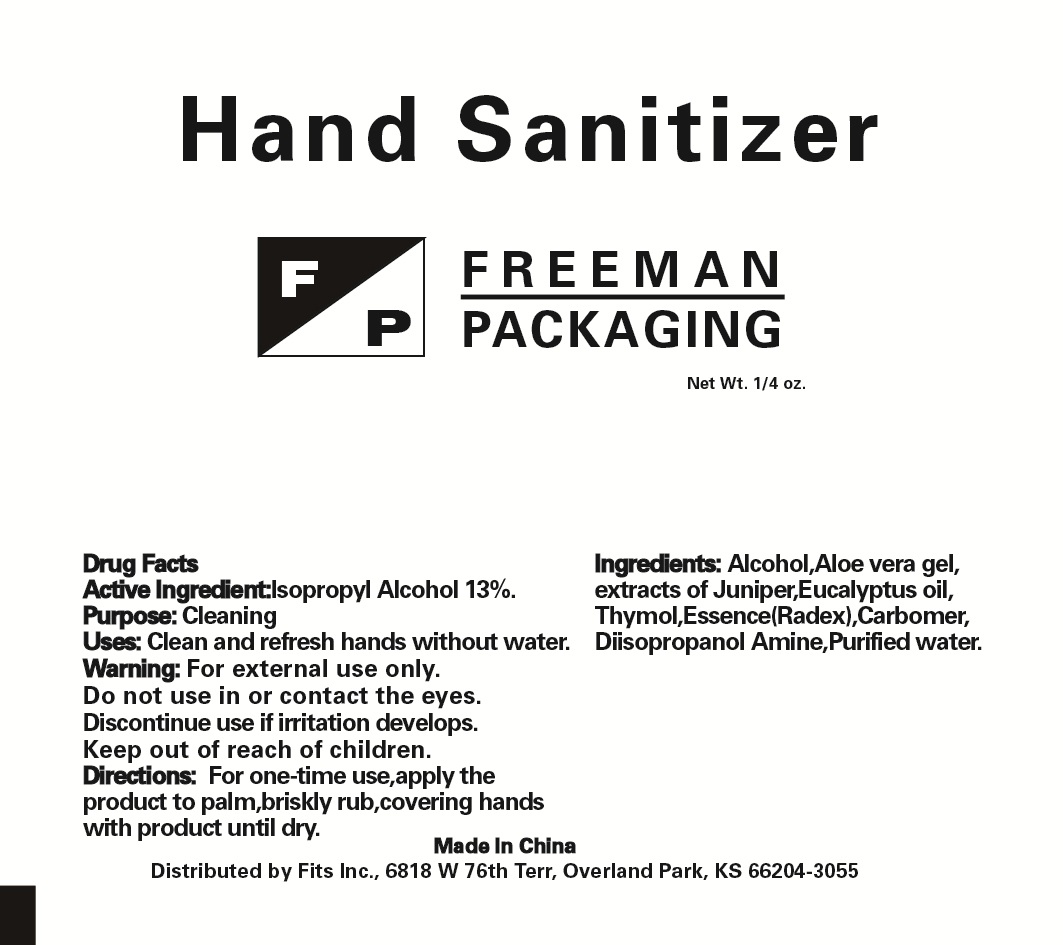 DRUG LABEL: Freeman Packing Hand Sanitizer 004
NDC: 67772-016 | Form: LIQUID
Manufacturer: Jiangxi Sencen Hygienic Products Co., Ltd.
Category: otc | Type: HUMAN OTC DRUG LABEL
Date: 20160717

ACTIVE INGREDIENTS: ISOPROPYL ALCOHOL 13 g/100 g
INACTIVE INGREDIENTS: WATER; ALCOHOL; ALOE VERA WHOLE; EUCALYPTUS OIL; THYMOL; JUNIPER TAR; CARBOMER 940; DIISOPROPANOLAMINE

Drug Fact

Active Ingredient

Isopropyl Alcohol........................13%

Purpose:

Cleaning

Uses:

Clean and refresh hands without water

Warnings:

May cause eye irritation. Keep out of eyes. Store in a cool place

Keep out of reach of children

Directions:

No water needed. Apply a small amount of product to dry skin. Rub briskly. Wipe with paper towel or clean cloth or rinse with water and dry.

STORAGE AND HANDLING

Store in a cool place

Inactive Ingredient:

Alcohol, Aloe Vera gel, Juniper Extract, Eucalyptus Oil, Thymol, Essence, Carbomer, Diisopropyl Amine, purified water